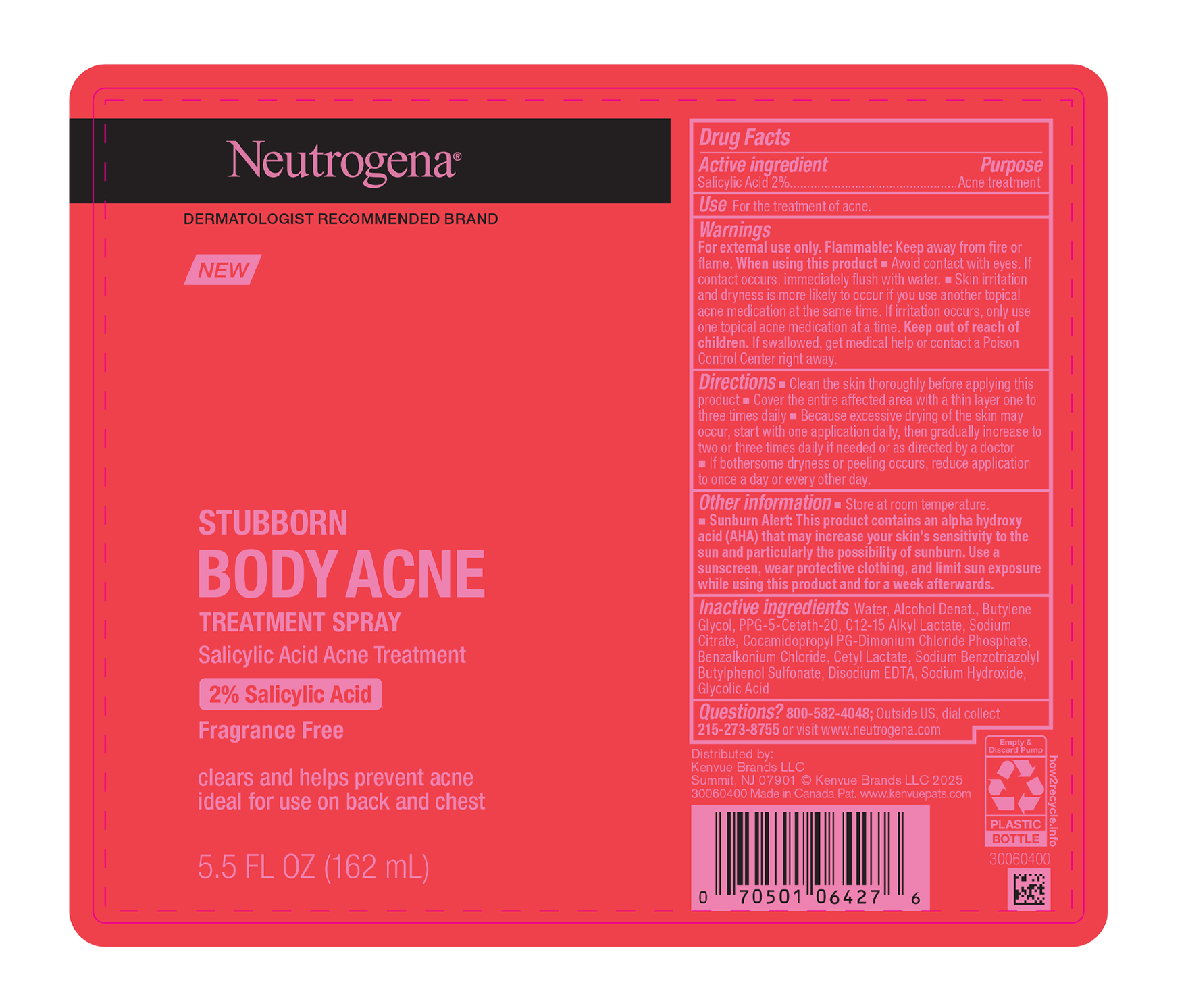 DRUG LABEL: Neutrogena Stubborn Body Acne Treatment
NDC: 69968-0758 | Form: SPRAY
Manufacturer: Kenvue Brands LLC
Category: otc | Type: HUMAN OTC DRUG LABEL
Date: 20250408

ACTIVE INGREDIENTS: SALICYLIC ACID 20 mg/1 mL
INACTIVE INGREDIENTS: ALCOHOL; BUTYLENE GLYCOL; SODIUM CITRATE; COCAMIDOPROPYL PG-DIMONIUM CHLORIDE PHOSPHATE; BENZALKONIUM CHLORIDE; WATER; PPG-5-CETETH-20; C12-15 ALKYL LACTATE; CETYL LACTATE; SODIUM BENZOTRIAZOLYL BUTYLPHENOL SULFONATE; EDETATE DISODIUM ANHYDROUS; SODIUM HYDROXIDE; GLYCOLIC ACID

Neutrogena Stubborn Body Acne Treatment Spray

Drug Facts

Active ingredient

Salicylic Acid 2%

Purpose

Acne treatment

Use

- For the treatment of acne

Warnings

For external use only. Flammable: Keep away from fire or flame.

When using this product

■ Avoid contact with eyes. If contact occurs, immediately flush with water.

■ Skin irritation and dryness is more likely to occur if you use another topical acne medication at the same time. If irritation occurs, only use one topical acne medication at a time.

Keep out of reach of children. If swallowed, get medical help or contact a Poison Control Center right away.

Directions

■ Clean the skin thoroughly before applying this product

■ Cover the entire affected area with a thin layer one to three times daily

■ Because excessive drying of the skin may occur, start with one application daily, then gradually increase to two or three times daily if needed or as directed by a doctor

■ If bothersome dryness or peeling occurs, reduce application to once a day or every other day.

Inactive ingredients

Water, Alcohol Denat., Butylene Glycol, PPG-5-Ceteth-20, C12-15 Alkyl Lactate, Sodium citrate, Cocamidopropyl PG-Dimonium Chloride Phosphate, Benzalkonium Chloride, Cetyl Lactate, Sodium Benzotriazolyl Butylphenol Sulfonate, Disodium EDTA, Sodium Hydroxide, Glycolic Acid

Other information

- Store at room temperature.
- Sunburn Alert: This product contains an alpha hydroxy acid (AHA) that may increase your skin's sensitivity to the sun and particularly the possibility of sunburn. Use a sunscreen, wear protective clothing, and limit sun exposure while using this product and for a week afterwards.

Questions?

800-582-4048; Outside US, dial collect 215-273-8755 or visit www.neutrogena.com

Distributed by:
Kenvue Brands LLC
Summit, NJ 07901

PRINCIPAL DISPLAY PANEL - 162 mL Bottle Label

Neutrogena®

DERMATOLOGIST RECOMMENDED BRAND

NEW

STUBBORN

BODY ACNE

TREATMENT SPRAY

Salicylic Acid Acne Treatment

2% Salicylic Acid

Fragrance Free

clears and helps prevent acne

ideal for use on back and chest

5.5 FL OZ (162mL)